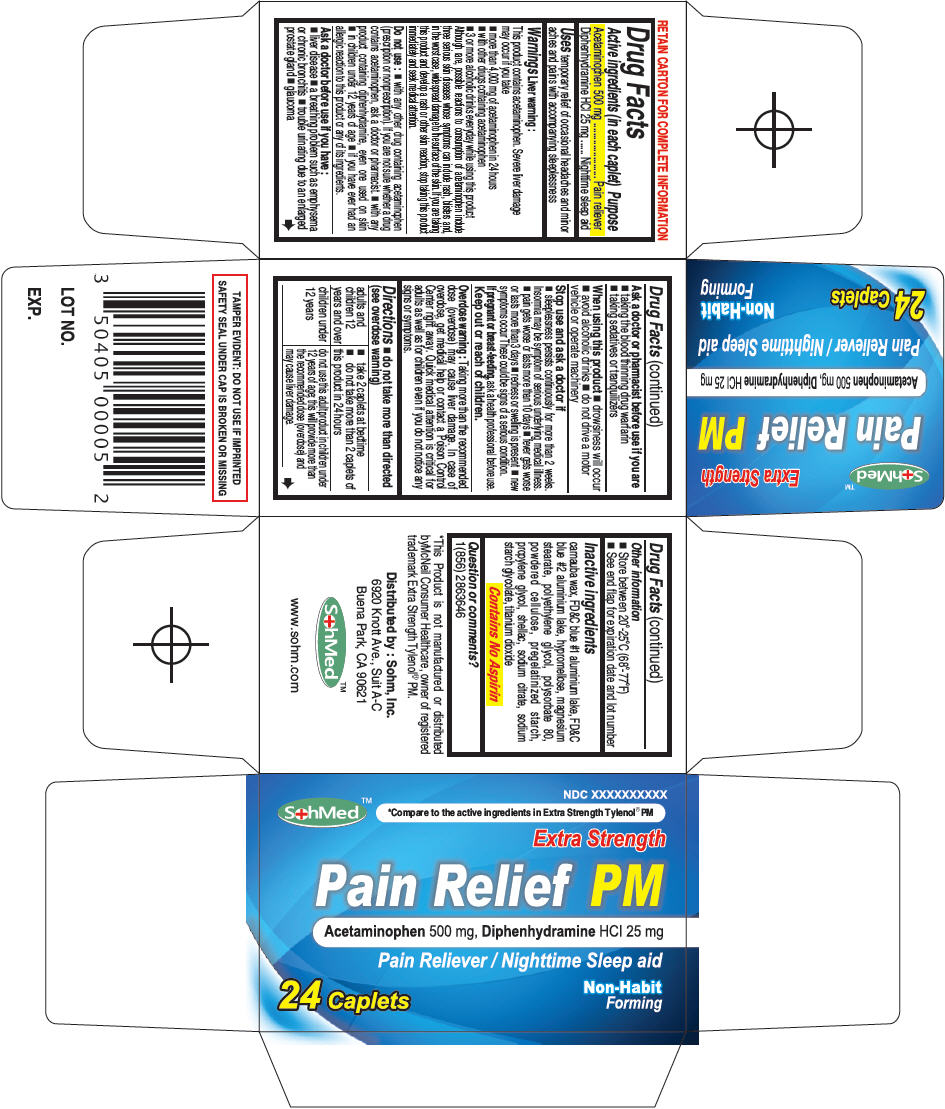 DRUG LABEL: SohMed Pain Relief PM
NDC: 50405-007 | Form: TABLET
Manufacturer: SOHM Inc.
Category: otc | Type: HUMAN OTC DRUG LABEL
Date: 20130822

ACTIVE INGREDIENTS: Acetaminophen 500 mg/1 1; Diphenhydramine Hydrochloride 25 mg/1 1
INACTIVE INGREDIENTS: CARNAUBA WAX; FD&C Blue No. 1; FD&C Blue No. 2; aluminum oxide; HYPROMELLOSES; MAGNESIUM STEARATE; POLYETHYLENE GLYCOL 6000; POLYSORBATE 80; POWDERED CELLULOSE; PROPYLENE GLYCOL; STARCH, CORN; SHELLAC; SODIUM CITRATE; SODIUM STARCH GLYCOLATE TYPE A CORN; TITANIUM DIOXIDE

SohMed™ Pain Relief PM

Drug Facts

ACTIVE INGREDIENT

Active ingredients (in each caplet) | Purpose
Acetaminophen 500 mg | Pain reliever
Diphenhydramine HCl 25 mg | Nighttime sleep aid

Uses

temporary relief of occasional headaches and minor aches and pains with accompanying sleeplessness

Warnings

Liver warning

This product contains acetaminophen. Severe liver damage may occur if you take

- more than 4,000 mg of acetaminophen in 24 hours
- with other drugs containing acetaminophen
- 3 or more alcoholic drinks everyday while using this product

Although rare, possible reactions to consumption of acetaminophen include three serious skin diseases whose symptoms can include rash, blisters and, in the worst case, widespread damage to the surface of the skin. If you are taking this product and develop a rash or other skin reaction, stop taking this product immediately and seek medical attention.

Do not use

- with any other drug containing acetaminophen (prescription or nonprescription). If you are not sure whether a drug contains acetaminophen, ask a doctor or pharmacist.
- with any product containing diphenhydramine, even one used on skin
- in children under 12 years of age
- if you have ever had an allergic reaction to this product or any of its ingredients.

Ask a doctor before use if you have

- liver disease
- a breathing problem such as emphysema or chronic bronchitis
- trouble urinating due to an enlarged prostate gland
- glaucoma

Ask a doctor or pharmacist before use if you are

- taking the blood thinning drug warfarin
- taking sedatives or tranquilizers

When using this product

- drowsiness will occur
- avoid alcoholic drinks
- do not drive a motor vehicle or operate machinery

Stop use and ask a doctor if

- sleeplessness persists continuously for more than 2 weeks. Insomnia may be symptom of serious underlying medical illness.
- pain gets worse or lasts more than 10 days
- fever gets worse or lasts more than 3 days
- redness or swelling is present
- new symptoms occur

These could be signs of a serious condition.

PREGNANCY OR BREAST FEEDING

If pregnant or breast-feeding, ask a health professional before use.

Keep out or reach of children.

Overdose warning

Taking more than the recommended dose (overdose) may cause liver damage. In case of overdose, get medical help or contact a Poison Control Center right away. Quick medical attention is critical for adults as well as for children even if you do not notice any signs or symptoms.

Directions

- do not take more than directed (see overdose warning)

adults and children 12 years and over | - take 2 caplets at bedtime - do not take more than 2 caplets of this product in 24 hours
children under 12 years | do not use this adult product in children under 12 years of age; this will provide more than the recommended dose (overdose) and may cause liver damage.

Other information

- Store between 20°-25°C (68°-77°F)
- See end flap for expiration date and lot number

Inactive ingredients

carnauba wax, FD&C blue #1 aluminium lake, FD&C blue #2 aluminium lake, hypromellose, magnesium stearate, polyethylene glycol, polysorbate 80, powdered cellulose, pregelatinized starch, propylene glycol, shellac, sodium citrate, sodium starch glycolate, titanium dioxide

Contains No Aspirin

Question or comments?

1(856) 2863646

Distributed by : Sohm, Inc.
6920 Knott Ave., Suit A-C
Buena Park, CA 90621

PRINCIPAL DISPLAY PANEL - 24 Caplet Bottle Carton

SohMed™

NDC XXXXXXXXXX

*Compare to the active ingredients in Extra Strength Tylenol® PM

Extra Strength

Pain Relief PM

Acetaminophen 500 mg, Diphenhydramine HCl 25 mg

Pain Reliever / Nighttime Sleep aid

24 Caplets

Non-Habit
Forming